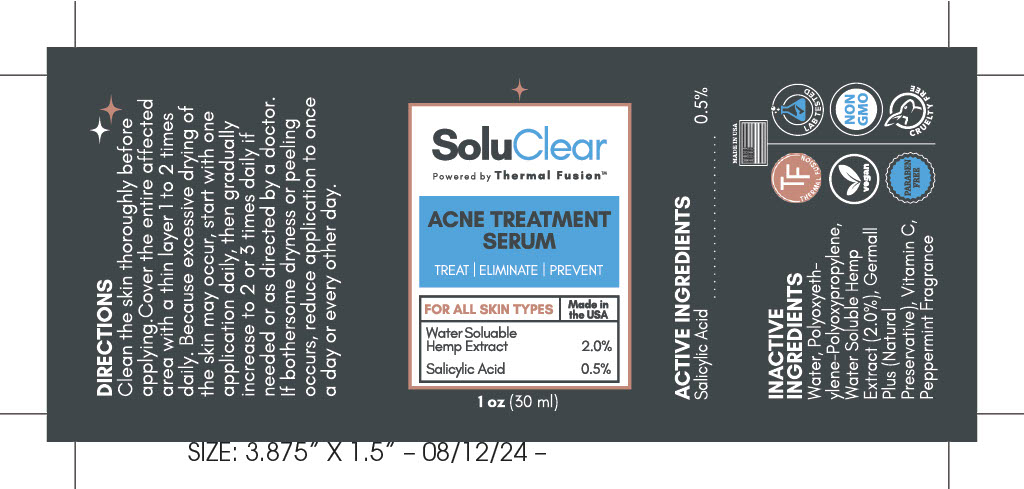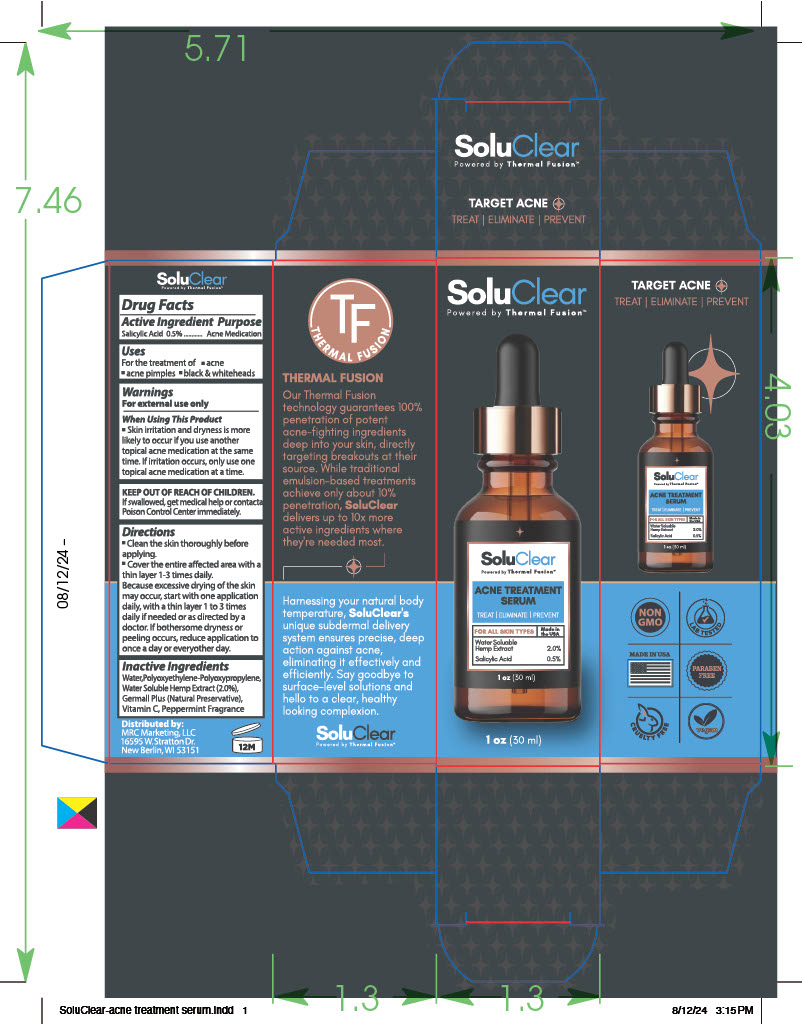 DRUG LABEL: SoluClear - Acne Treatment Serum
NDC: 83696-100 | Form: GEL
Manufacturer: Respect Manufacturing Corporation
Category: otc | Type: HUMAN OTC DRUG LABEL
Date: 20250623

ACTIVE INGREDIENTS: SALICYLIC ACID 0.15 g/30 g
INACTIVE INGREDIENTS: HEMP; PROPYLENE GLYCOL; FRAGRANCE PEPPERMINT ORC2000647; WATER; DIAZOLIDINYL UREA; ASCORBIC ACID; IODOPROPYNYL BUTYLCARBAMATE; PEG/PPG-4/30 COPOLYMER

SoluClear Acne Treatment Serum

ACTIVE INGREDIENT

Salicylic Acid 0.5%

PURPOSE

Acne Medication

WARNINGS

For external use only

WHEN USING

• Skin irritation and dryness is more likely to occur if you use another topical acne medication at the same time. If irritation occurs, only use one topical acne medication at a time.

KEEP OUT OF REACH OF CHILDREN

If swallowed get medical help or contact a Poison Control Center immediately.

DOSAGE AND ADMINISTRATION

- Clean the skin thoroughly before applying
- Cover the entire affected area with a thin layer 1-3 times daily. Because excessive drying of the skin may occur, start with one application daily, with a thin layer 1-3 times daily if needed or as directed by doctor. If bothersome dryness or peeling occurs, reduce application to once a day or everyother day.

INACTIVE INGREDIENT

Water, Polyoxyethylene-Polyoxypropylene, Water Soluable Hemp Extract (2.0%), Germall Plus (natural preservative), Vitamin C, Peppermint Fragrance

Uses

For the treatment of • acne • acne pimples • black & whiteheads

PACKAGE LABEL

Front Panel

SoluClear

Powered by Thermal Fusion

Acne Treatment Serum

Treat Eliminate Prevent

For all Skin Types

Made in the USA

Water Soluable Hemp Extract 2.0%

Salicylic Acid 0.5%

1 oz (30 ml)

Side Panels

Thermal Fusion

Our thermal fusion technology guarantees 100% penetration of potent acne-fighting ingredients deep into your skin, directly targeting breakouts at their source. While traditional emulsion-based treatments achieve only about 10% penetration, SoluClear delivers up to 10x more active ingredients where they-re needed most.

Harnessing your natural body temperature, Soluclear's unique subdermal delivery system ensures precise, deep action against acne, eliminating it effectively and efficiently. Say goodbye to surface-level solutions and hello to a clear, healthy looking complexion.

Target Acne

Treat Eliminate Prevent

Non GMO

Lab Tested

Made in USA

Paraben Free

Cruelty Free

Vegan

Back

Distributed by:

MRC Marketing, LLC

16595 W. Stratton Dr.

New Berlin, WI 53151